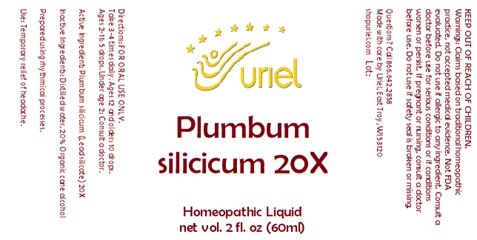 DRUG LABEL: Plumbum silicicum 20
NDC: 48951-8441 | Form: LIQUID
Manufacturer: Uriel Pharmacy Inc.
Category: homeopathic | Type: HUMAN OTC DRUG LABEL
Date: 20251119

ACTIVE INGREDIENTS: LEAD MONOSILICATE 20 [hp_X]/1 mL
INACTIVE INGREDIENTS: WATER; ALCOHOL

Plumbum silicicum 20

INDICATIONS AND USAGE

Directions: FOR ORAL USE ONLY.

DOSAGE AND ADMINISTRATION

Take 3-4 times daily. Ages 12 and older: 10 drops. Ages 2-11: 5 drops. Under age 2: Consult a doctor.

Active Ingredient: Plumbum silicicum 20X (Lead silicate)

Inactive Ingredients: Distilled water, 20% Organic cane alcohol

Prepared using rhythmical processes.

PURPOSE

Use: Temporary relief of headache.

KEEP OUT OF REACH OF CHILDREN.

WARNINGS

Warnings: Claims based on traditional homeopathic practice, not accepted medical evidence. Not FDA evaluated. Do not use if allergic to any ingredient. Consult a doctor before use for serious conditions or if conditions worsen or persist. If pregnant or nursing, consult a doctor before use. Do not use if safety seal is broken or missing.

Questions? Call 866.642.2858
Made with care by Uriel, East Troy, WI 53120
shopuriel.com